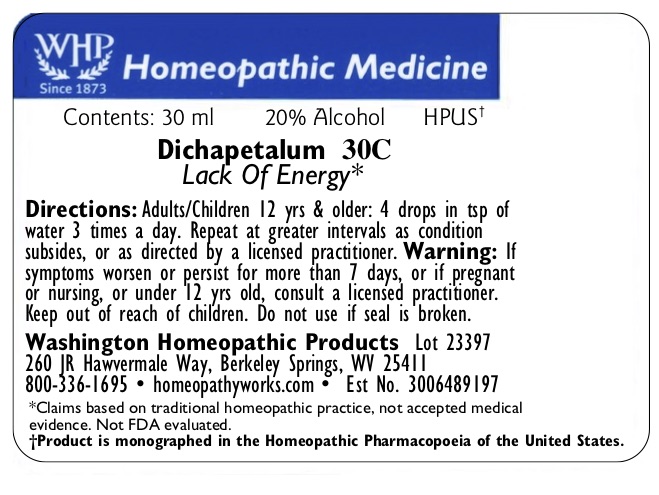 DRUG LABEL: Dichapetalum
NDC: 71919-254 | Form: LIQUID
Manufacturer: Washington Homeopathic Products
Category: homeopathic | Type: HUMAN OTC DRUG LABEL
Date: 20181231

ACTIVE INGREDIENTS: DICHAPETALUM MADAGASCARIENSE BARK/LEAF 30 [hp_C]/1 mL
INACTIVE INGREDIENTS: ALCOHOL; WATER

DRUG FACTS

ACTIVE INGREDIENTS

DICHAPETALUM

USES

To relieve the symptoms of lack of energy.

KEEP OUT OF REACH OF CHILDREN

Keep this and all medicines out of reach of children.

INDICATIONS

DICHAPETALUM Lack of energy

STOP USE AND ASK DOCTOR

If symptoms persist/worsen or if pregnant/nursing, consult your practitioner.

DIRECTIONS

Adults: 4 drops into a tsp. of water 3 times a day. Children: 1/2 dose. Repeat at greater intervals as condition subsides. Or as directed bya lic. practitioner.

INACTIVE INGREDIENTS

Sucrose/Lactose

PRINCIPAL DISPLAY PANEL

The OTC potency range of DICHAPETALUM is 2x–30x, 1c–30c, 200c, 1m, 10m, 50m, and CM.
Availability is subject to change.

All WHP single remedies are made to order; thus, the labels are printed on the same label stock, as the orders are filled.

‘Bottle Size,’ ‘Potency,’ and ‘Alcohol Percentage’ vary on the label depending on customer choice.

Standard bottle sizes for dilution-form remedies are 15ml, 30ml, 50ml, and 100ml.